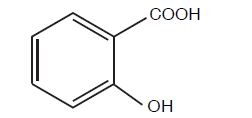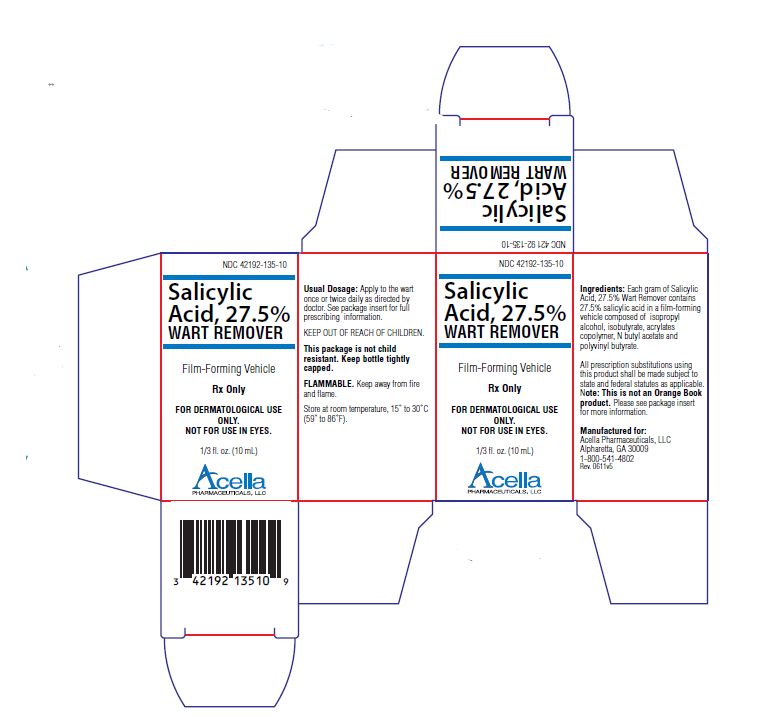 DRUG LABEL: SALICYLIC ACID
NDC: 42192-135 | Form: LIQUID
Manufacturer: Acella Pharmaceuticals, LLC
Category: prescription | Type: HUMAN PRESCRIPTION DRUG LABEL
Date: 20240111

ACTIVE INGREDIENTS: SALICYLIC ACID 275 mg/1 mL
INACTIVE INGREDIENTS: ISOPROPYL ALCOHOL; BUTYL ACETATE

Salicylic Acid, 27.5%

Wart Remover

Rx Only

FOR TOPICAL USE ONLY. NOT FOR OPHTHALMIC, ORAL OR INTRAVAGINAL USE.

DESCRIPTION:

Salicylic Acid, 27.5% Wart Remover is a topical preparation containing 27.5% salicylic acid in a film-forming vehicle composed of isopropyl alcohol, isobutyrate, acrylates copolymer, N butyl acetate and polyvinyl butyrate. The pharmacologic activity of Salicylic Acid, 27.5% Wart Remover is generally attributed to the keratolytic activity of salicylic acid which is incorporated into a film-forming vehicle designed to cover the wart without the need for a bandage. The structural formula of salicylic acid is:

CLINICAL PHARMACOLOGY:

Although the exact mode of action for salicylic acid in the treatment of warts is not known, its activity appears to be associated with its keratolytic action which results in mechanical removal of epidermal cells infected with wart viruses.

INDICATIONS AND USES:

Salicylic Acid, 27.5% Wart Remover is indicated for the topical treatment and removal of common warts and plantar warts.

CONTRAINDICATIONS:

Salicylic Acid, 27.5% Wart Remover should not be used by diabetics or patients with impaired blood circulation. Salicylic Acid, 27.5% Wart Remover should not be used on moles, birthmarks, unusual warts with hair growing from them or warts on the face.

PRECAUTIONS:

Salicylic Acid, 27.5% Wart Remover is for external use only. Do not permit Salicylic Acid, 27.5% Wart Remover to contact eyes or mucous membranes. If contact with eyes or mucous membranes occurs, immediately flush with water for 15 minutes. Salicylic Acid, 27.5% Wart Remover should not be allowed to contact normal skin surrounding wart. Treatment should be discontinued if excessive irritation occurs. Salicylic Acid, 27.5% Wart Remover is flammable and should be kept away from fire or flame. Keep bottle tightly capped when not in use.

KEEP THIS AND ALL MEDICATIONS OUT OF THE REACH OF CHILDREN.

ADVERSE REACTIONS:

A localized irritant reaction may occur if Salicylic Acid, 27.5% Wart Remover is applied to the normal skin surrounding the wart. Any irritation may normally be controlled by temporarily discontinuing use and by applying the medication only to the wart site when treatment is resumed.

DOSAGE AND ADMINISTRATION:

Prior to application of Salicylic Acid, 27.5% Wart Remover, soak wart in warm water for five minutes. Remove any loosened tissue by gently rubbing with a brush, wash cloth or emery board. Dry thoroughly. Using the brush applicator supplied, apply twice to entire wart surface, allowing the first application to dry before applying the second. Treatment should be once or twice a day and should continue as directed by physician. Be careful not to apply to surrounding skin.

Clinically visible improvement will normally occur during the first or second week of therapy. Maximum resolution may be expected after four to six weeks of use.

HOW SUPPLIED:

Salicylic Acid, 27.5% Wart Remover is supplied in 10 mL amber bottles with a brush applicator, (NDC 42192-135-10).

STORAGE AND HANDLING

Store at controlled room temperature, 15º - 30º (59º - 86ºF).

MANUFACTURED FOR:
Acella Pharmaceuticals, LLC
Alpharetta, GA 30009
1-800-541-4802
Rev. 0611

PATIENT INSTRUCTIONS:

Your health care provider has prescribed Salicylic Acid, 27.5% Wart Remover, a topical prescription preparation for the treatment of common and plantar warts. In order for Salicylic Acid, 27.5% Wart Remover to work correctly and to ensure maximum benefit, the following instructions should be followed carefully. Of course, as with any medication, always consult your health care provider if you experience any discomfort or unexpected reactions.

STEP 1: WASH

- Soak wart area in warm water for about 5 minutes.
- Remove any loose tissue using a wash cloth, emery board or pumice stone.
- Dry thoroughly.

STEP 2: BRUSH

- Using the brush applicator supplied, apply twice to entire wart surface, allowing the first application to dry before applying the second.
- Be careful not to apply to surrounding skin.
- Leave Salicylic Acid, 27.5% Wart Remover on wart area after it dries.

Repeat Step 1 and Step 2 once or twice daily as advised by your health care provider.

Clinically visible improvement will normally occur during the first or second week of therapy.

MANUFACTURED FOR:
Acella Pharmaceuticals, LLC
Alpharetta, GA 30009
1-800-541-4802

Rev. 0611

PRINCIPAL DISPLAY PANEL - 10 mL

NDC 42192-135-10

Salicylic
Acid, 27.5%
WART REMOVER

Film-Forming Vehicle

Rx Only

FOR DERMATOLOGICAL USE
ONLY.
NOT FOR USE IN EYES.

1/3 fl. oz. (10 mL)

Acella
PHARMACEUTICALS, LLC.